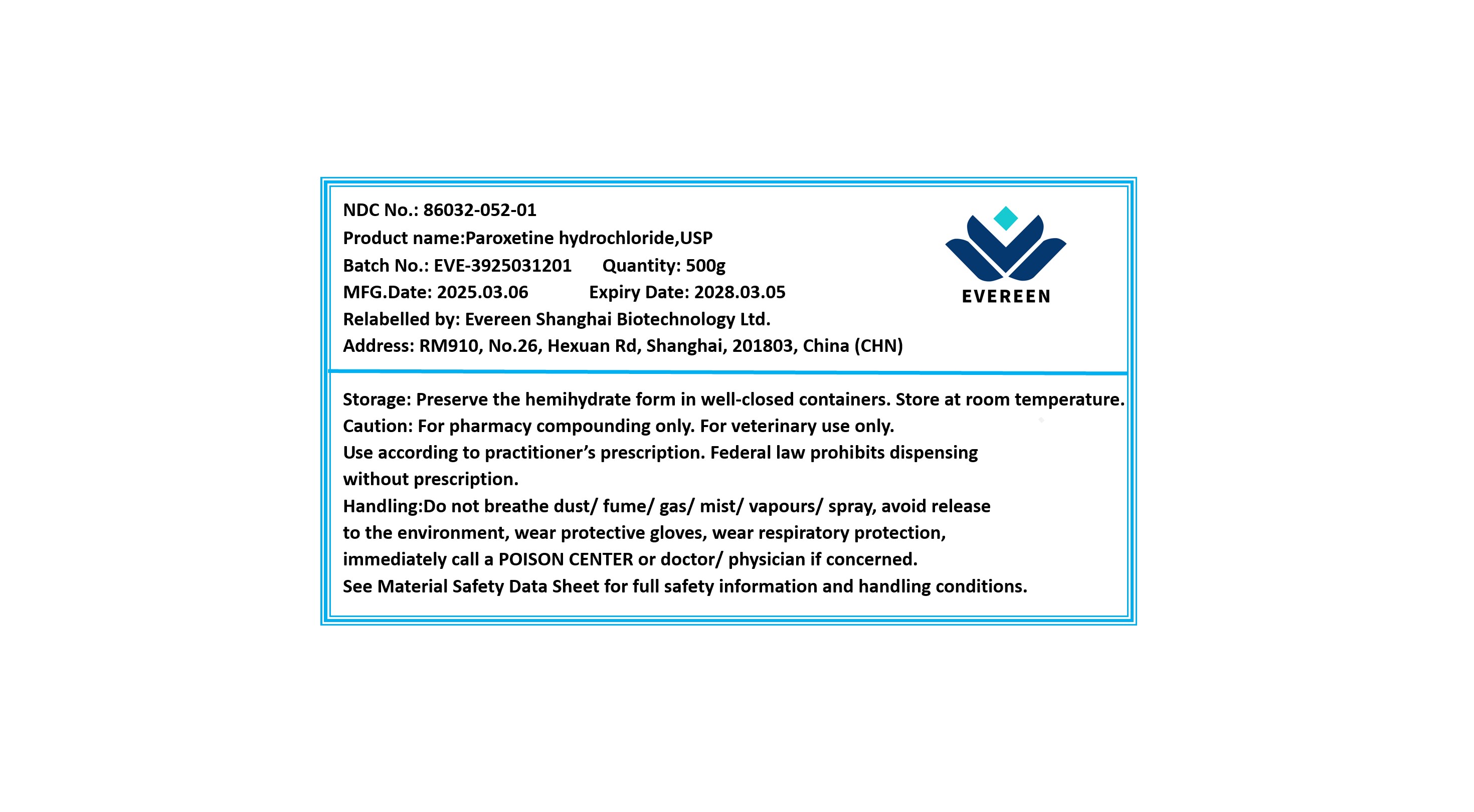 DRUG LABEL: Paroxetine hydrochloride
NDC: 86032-052 | Form: POWDER
Manufacturer: Evereen Shanghai Biotechnology Ltd.
Category: other | Type: BULK INGREDIENT - ANIMAL DRUG
Date: 20250912

ACTIVE INGREDIENTS: PAROXETINE HYDROCHLORIDE 1 g/1 g

Paroxetine hydrochloride